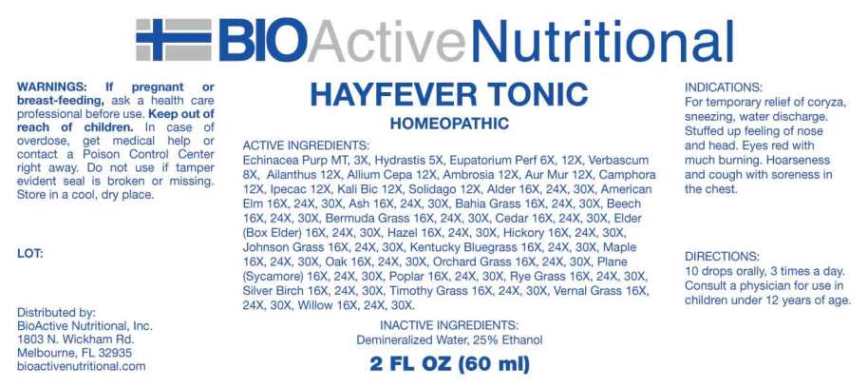 DRUG LABEL: Hayfever Tonic
NDC: 43857-0611 | Form: LIQUID
Manufacturer: BioActive Nutritional, Inc.
Category: homeopathic | Type: HUMAN OTC DRUG LABEL
Date: 20241017

ACTIVE INGREDIENTS: ECHINACEA PURPUREA WHOLE 1 [hp_X]/1 mL; GOLDENSEAL 5 [hp_X]/1 mL; EUPATORIUM PERFOLIATUM FLOWERING TOP 6 [hp_X]/1 mL; VERBASCUM THAPSUS WHOLE 8 [hp_X]/1 mL; AILANTHUS ALTISSIMA FLOWERING TWIG 12 [hp_X]/1 mL; ONION 12 [hp_X]/1 mL; AMBROSIA ARTEMISIIFOLIA WHOLE 12 [hp_X]/1 mL; GOLD TRICHLORIDE 12 [hp_X]/1 mL; CAMPHOR (NATURAL) 12 [hp_X]/1 mL; IPECAC 12 [hp_X]/1 mL; POTASSIUM DICHROMATE 12 [hp_X]/1 mL; SOLIDAGO VIRGAUREA FLOWERING TOP 12 [hp_X]/1 mL; POA PRATENSIS POLLEN 16 [hp_X]/1 mL; DACTYLIS GLOMERATA POLLEN 16 [hp_X]/1 mL; CYNODON DACTYLON POLLEN 16 [hp_X]/1 mL; SORGHUM HALEPENSE POLLEN 16 [hp_X]/1 mL; LOLIUM PERENNE POLLEN 16 [hp_X]/1 mL; ANTHOXANTHUM ODORATUM 16 [hp_X]/1 mL; PASPALUM NOTATUM POLLEN 16 [hp_X]/1 mL; PHLEUM PRATENSE POLLEN 16 [hp_X]/1 mL; ULMUS AMERICANA POLLEN 16 [hp_X]/1 mL; PLATANUS X ACERIFOLIA POLLEN 16 [hp_X]/1 mL; FRAXINUS EXCELSIOR POLLEN 16 [hp_X]/1 mL; FAGUS SYLVATICA POLLEN 16 [hp_X]/1 mL; SALIX X FRAGILIS POLLEN 16 [hp_X]/1 mL; ACER NEGUNDO POLLEN 16 [hp_X]/1 mL; ALNUS RUBRA POLLEN 16 [hp_X]/1 mL; JUNIPERUS VIRGINIANA POLLEN 16 [hp_X]/1 mL; ACER SACCHARUM POLLEN 16 [hp_X]/1 mL; CORYLUS AVELLANA POLLEN 16 [hp_X]/1 mL; POPULUS ALBA POLLEN 16 [hp_X]/1 mL; BETULA PENDULA POLLEN 16 [hp_X]/1 mL; QUERCUS ROBUR POLLEN 16 [hp_X]/1 mL; CARYA GLABRA POLLEN 16 [hp_X]/1 mL
INACTIVE INGREDIENTS: WATER; ALCOHOL

DRUG FACTS:

ACTIVE INGREDIENTS:

Echinacea Purpurea MT, 3X, Hydrastis Canadensis 5X, Eupatorium Perfoliatum 6X, 12X, Verbascum Thapsus 8X, Ailanthus Glandulosus 12X, Allium Cepa 12X, Ambrosia Artemisiaefolia 12X, Aurum Muriaticum 12X, Camphora 12X, Ipecacuanha 12X, Kali Bichromicum 12X, Solidago Virgaurea 12X, Kentucky Bluegrass 16X, 24X, 30X, Orchard Grass16X, 24X, 30X, Bermuda Grass 16X, 24X, 30X, Johnson Grass 16X, 24X, 30X, Rye Grass 16X, 24X, 30X, Vernal Grass 16X, 24X, 30X, Bahia Grass 16X, 24X, 30X, Timothy Grass 16X, 24X, 30X, American Elm 16X, 24X, 30X, Plane (Sycamore) 16X, 24X, 30X, Ash 16X, 24X, 30X, Beech 16X, 24X, 30X, Willow 16X, 24X, 30X, Elder (Box Elder) 16X, 24X, 30X, Alder 16X, 24X, 30X, Cedar 16X, 24X, 30X, Maple 16X, 24X, 30X, Hazel 16X, 24X, 30X, Poplar 16X, 24X, 30X, Silver Birch 16X, 24X, 30X, Oak 16X, 24X, 30X, Hickory 16X, 24X, 30X.

INDICATIONS:

For temporary relief of coryza, sneezing, water discharge. Stuffed up feeling of nose and head. Eyes red with much burning. Hoarseness and cough with soreness in the chest.

WARNINGS:

If pregnant or breast-feeding, ask a health care professional before use.

Keep out of reach of children. In case of overdose, get medical help or contact a Poison Control Center right away.

Do not use if tamper evident seal is broken or missing.

Store in a cool, dry place.

Keep out of reach of children. In case of overdose, get medical help or contact a Poison Control Center right away.

DIRECTIONS:

10 drops orally, 3 times a day. Consult a physician for use in children under 12 years of age.

INDICATIONS:

For temporary relief of coryza, sneezing, water discharge. Stuffed up feeling of nose and head. Eyes red with much burning. Hoarseness and cough with soreness in the chest.

INACTIVE INGREDIENTS:

Demineralized Water, 25% Ethanol

QUESTIONS:

Distributed by:

BioActive Nutritional, Inc.

1803 N. Wickham Rd.

Melbourne, FL 32935

bioactivenutritional.com

PACKAGE LABEL DISPLAY:

BIOActive Nutritional
HAYFEVER TONIC

HOMEOPATHIC

2 FL OZ (60 ml)